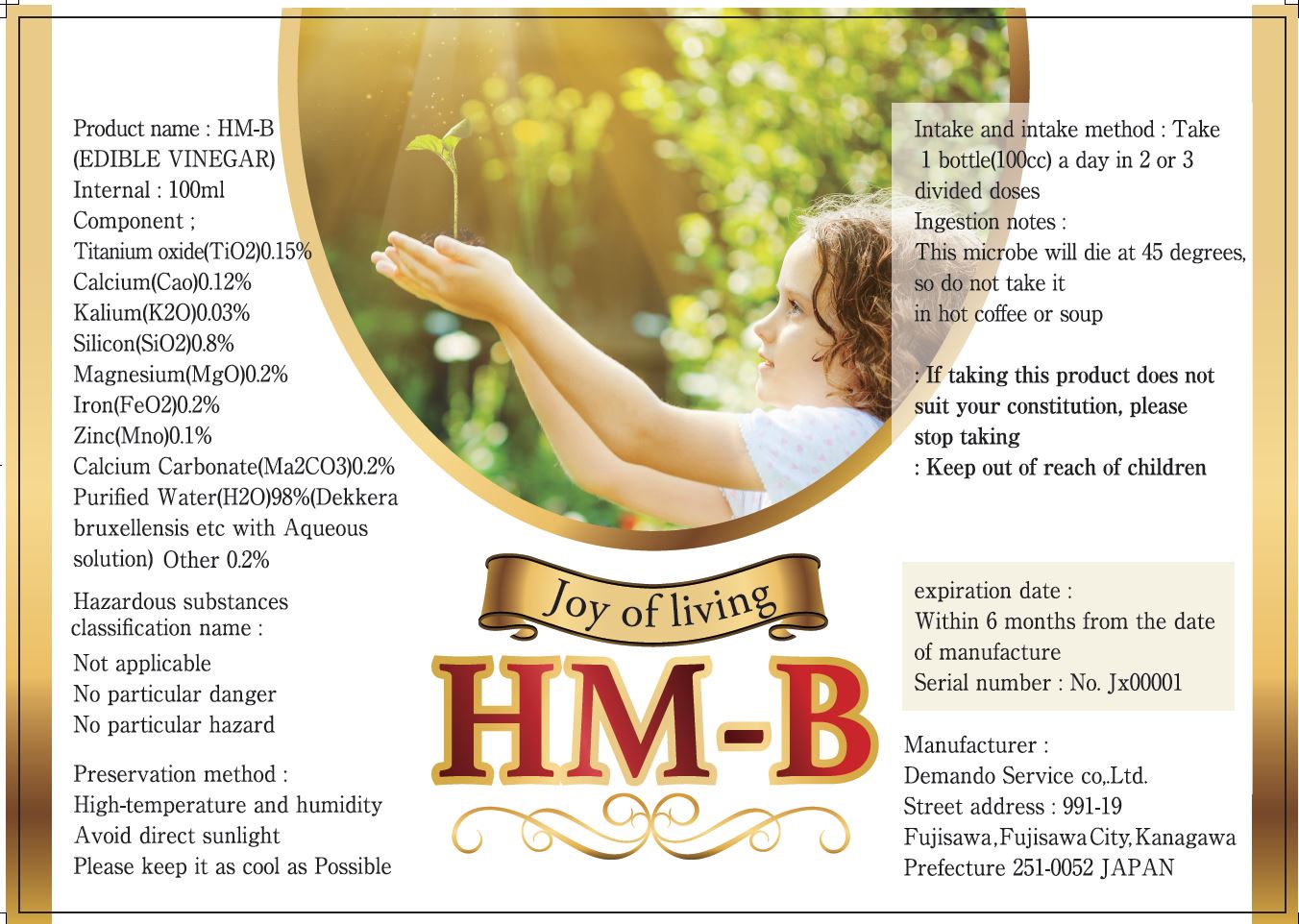 DRUG LABEL: HM-B (EDIBLE VINEGAR)
NDC: 73474-0001 | Form: LIQUID
Manufacturer: DEMAND SERVICE, CO., LTD.
Category: otc | Type: HUMAN OTC DRUG LABEL
Date: 20241225

ACTIVE INGREDIENTS: TITANIUM DIOXIDE 2 g/100 mL
INACTIVE INGREDIENTS: WATER; CALCIUM

Drug Facts

ACTIVE INGREDIENT

titanium oxide (titanium dioxide)

INACTIVE INGREDIENT

Calcium(Cao)0.12% Kalium(K2O)0.03%, Silicon(SiO2)0.8% Magnesium(MgO)0.2%, Iron(FeO2)0.2% Zinc(Mno)0.1%
Calcium Cardonate(Ma2CO3)0.2%, Purified Water(H2O)98%(Dekkerabruxellensisetc with Aqueous solution) Other 0.2%

PURPOSE

Promoting health, strengthening immunity

keep out of reach of the children

INDICATIONS AND USAGE

Take 1 bottle(100cc) a day in 2 or 3 divided doses

WARNINGS

This microbe will die at 45 degrees, so do not take it in hot coffee or soup

If taking this product does not suit your constitution, please stop taking

DOSAGE AND ADMINISTRATION

for oral use only